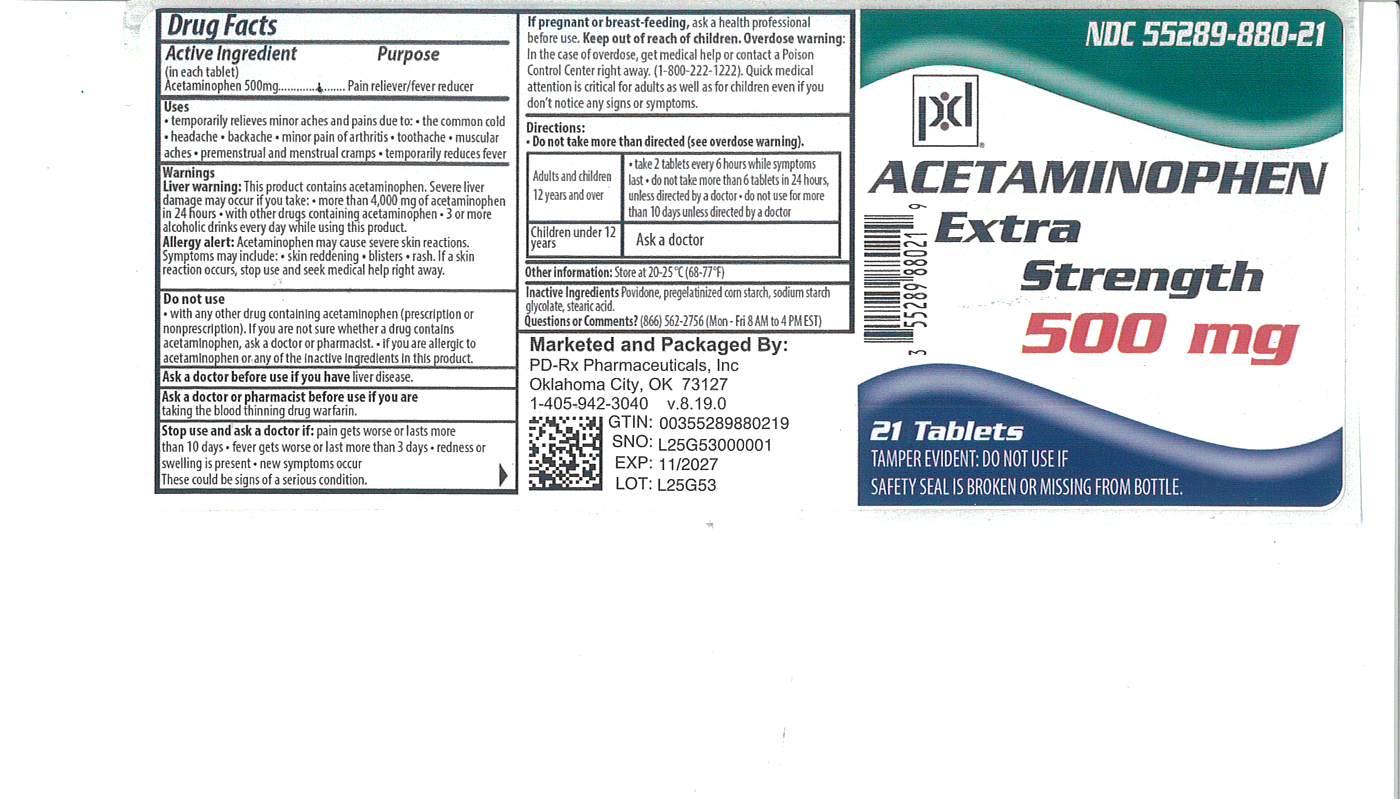 DRUG LABEL: Acetaminophen
NDC: 55289-880 | Form: TABLET
Manufacturer: PD-Rx Pharmaceuticals, Inc.
Category: otc | Type: HUMAN OTC DRUG LABEL
Date: 20260112

ACTIVE INGREDIENTS: ACETAMINOPHEN 500 mg/1 1
INACTIVE INGREDIENTS: POVIDONE, UNSPECIFIED; STARCH, CORN; SODIUM STARCH GLYCOLATE TYPE A POTATO; STEARIC ACID

Acetaminophen Extra Stength Tablet

Active ingredient (in each tablet)

Acetaminophen 500 mg

Purpose

Pain reliever/fever reducer

Uses

- temporarily relieves minor aches and pains due to:
- the common cold
- headache
- backache
- minor pain of arthritis
- toothache
- muscular aches
- premenstrual and menstrual cramps
- temporarily reduces fever

Warnings

Liver warning: This product contains acetaminophen. Severe liver damage may occur if you take

- more than 4000 mg of acetaminophen in 24 hours
- with other drugs containing acetaminophen
- 3 or more alcoholic drinks every day while using this product

Allergy alert: acetaminophen may cause severe skin reactions. Symptoms may include:

- skin reddening
- blisters
- rash

If a skin reaction occurs, stop use and seek medical help right away.

Do not use

- with any other drug containing acetaminophen (prescription or nonprescription). If you are not sure whether a drug contains acetaminophen, ask a doctor or pharmacist
- if you are allergic to acetaminophen or any of the inactive ingredients in this product

Ask a doctor before use if you have

liver disease.

Ask a doctor or pharmacist before use if you are

taking the blood thinning drug warfarin.

Stop use and ask a doctor if

- pain gets worse or lasts more than 10 days
- fever gets worse or lasts more than 3 days
- redness or swelling is present
- new symptoms occur

These could be signs of a serious condition.

If pregnant or breast-feeding,

ask a health professional before use.

Keep out of reach of children.

Overdose warning: In case of overdose, get medical help or contact a Poison Control Center right away (1-800-222-1222). Quick medical attention is critical for adults as well as for children even if you don't notice any signs or symptoms.

Directions

- do not take more than directed (see overdose warning).

adult and children 12 years and over | - take 2 tablets, every 4 to 6 hours while symptoms last - do not take more than 6 tablets in 24 hours, unless directed by a doctor - do not use for more than 10 days unless directed by a doctor
children under 12 years | Ask a doctor

Other information

- store between 20-25^0C (68-77^0F)

Inactive ingredients

povidone, pregelatinized corn starch, sodium starch glycolate, stearic acid

Questions or comments?

(866)-562-2756 (Mon - Fri 8 AM to 4 PM EST)

PACKAGE LABEL

Acetaminophen 500mg

TAMPER EVIDENT: DO NOT USE IF SAFETY SEAL IS BROKEN OR MISSING FROM BOTTLE.